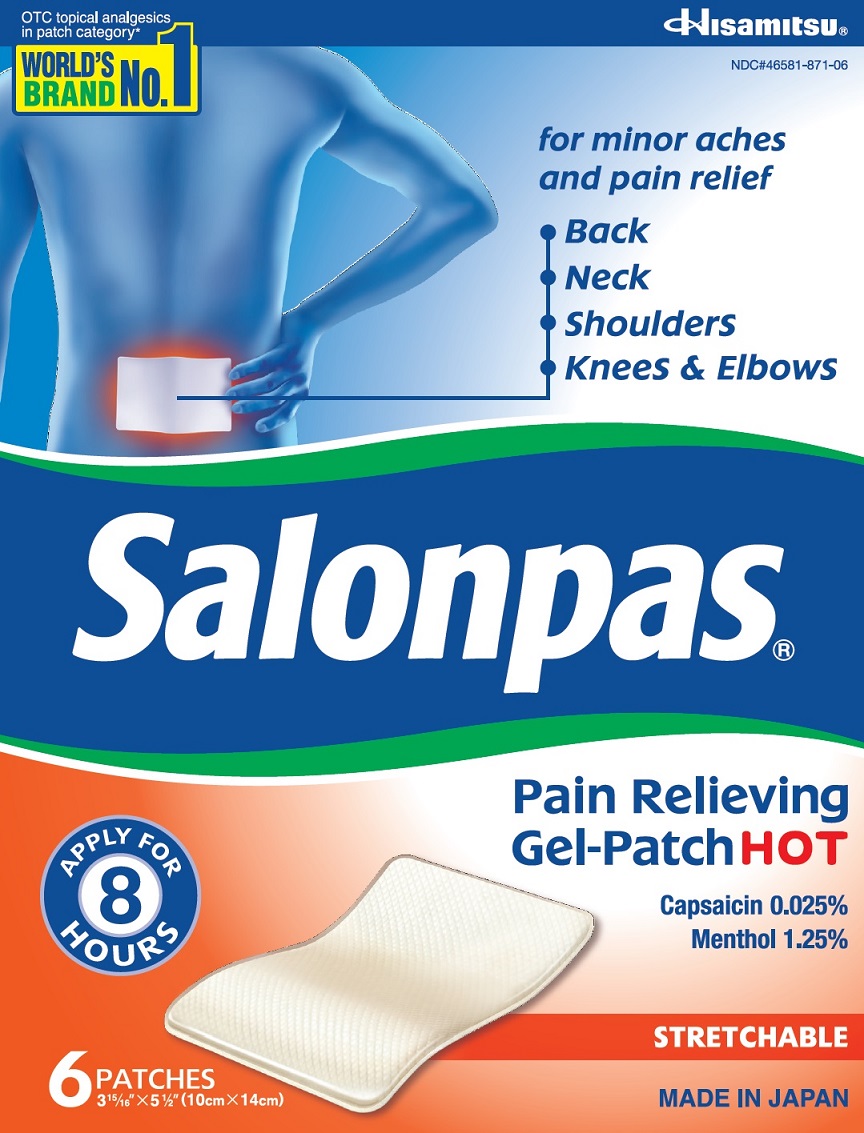 DRUG LABEL: Salonpas
NDC: 46581-871 | Form: PATCH
Manufacturer: Hisamitsu Pharmaceutical Co., Inc.
Category: otc | Type: HUMAN OTC DRUG LABEL
Date: 20251215

ACTIVE INGREDIENTS: CAPSICUM 0.025 g/100 g; MENTHOL 1.25 g/100 g
INACTIVE INGREDIENTS: EDETATE DISODIUM; GELATIN, UNSPECIFIED; GLYCERIN; SILODRATE; OLEYL ALCOHOL; POLYVINYL ALCOHOL, UNSPECIFIED; PROPYLENE GLYCOL; SORBITAN MONOOLEATE; TARTARIC ACID; TITANIUM DIOXIDE; WATER

Active ingredients

Capsicum extract 0.025% as Capsaicin
Menthol 1.25%

Purpose

Topical analgesic

Uses

For temporary relief of minor aches and pains of muscles and joints associated with:

- simple backache
- arthritis
- strains
- bruises
- sprains

Warnings

For external use only

Do not use

- on wounds or damaged skin
- with a heating pad
- if you are allergic to any ingredients of this product

When using this product

- use only as directed
- avoid contact with the eyes, mucous membranes or rashes
- do not bandage tightly
- discontinue use at least 1 hour before a bath or shower
- do not use immediately after a bath or shower

Stop use and ask a doctor if

- skin reactions such as redness, itching, rash, excessive irritation, buring sensation, swelling or blistering occur
- conditions worsen
- symptoms persist for more than 7 days
- symptoms clear up and occur again within a few days

If pregnant or breast-feeding,

ask a health professional before use.

Keep out of reach of children.

If swallowed, get medical help or contact a Poison Control Center right away.

Directions

Adults and children 12 years of age and over:

- clean and dry affected area
- remove film from patch and apply to the skin (see illustration)
- apply to affected area not more than 3 to 4 times daily
- remove patch from the skin after at most 8 hour-application

Children under 12 years of age: consult a doctor

Other information

- Avoid storing product in direct sunlight
- Protect product from excessive moisture

Inactive ingredients

edetate disodium, gelatin, glycerin, magnesium aluminometasilicate, methylacrylate/2-ethylhexyl acrylate copolymer, nonoxynol, oleyl alcohol, polyacrylic acid, polyvinyl alcohol, propylene glycol, sodium polyacrylate, sorbitan monooleate, tartaric acid, titanium dioxide, water

Questions or comments?

Toll free 1-800-826-8861 www.salonpas.us

Principal Display Panel

OTC topical analgesics in patch category*
WORLD'S BRAND NO.1

Hisamitsu

NDC#46581-871-06

for minor aches and pain relief

Back
Neck
Shoulders
Knees and Elbows
Salonpas Pain Relieving Gel-Patch HOT

Capsaicin 0.025%
Menthol 1.25%

APPLY FOR 8 HOURS

STRETCHABLE

6 PATCHES 3 15/16" X 5 1/2" (10cm X 14cm)

MADE IN JAPAN